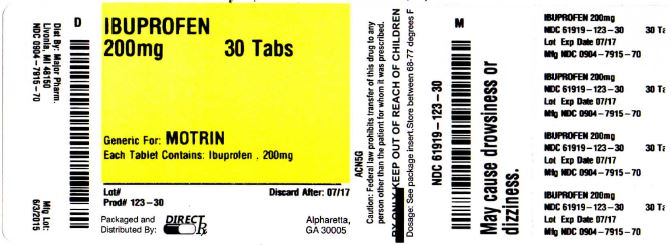 DRUG LABEL: IBUPROFEN
NDC: 61919-123 | Form: TABLET, FILM COATED
Manufacturer: DIRECT RX
Category: otc | Type: HUMAN OTC DRUG LABEL
Date: 20151103

ACTIVE INGREDIENTS: IBUPROFEN 200 mg/1 1
INACTIVE INGREDIENTS: HYPROMELLOSES; LACTOSE; MAGNESIUM STEARATE; CELLULOSE, MICROCRYSTALLINE; POLYDEXTROSE; POLYETHYLENE GLYCOLS; SODIUM STARCH GLYCOLATE TYPE A POTATO; STEARIC ACID

IBUPROFEN

OTC - ACTIVE INGREDIENT SECTION

Ibuprofen USP, 200 mg (NSAID)*

*nonsteroidal anti-inflammatory drug

OTC - PURPOSE SECTION

Pain reliever/fever reducer

INDICATIONS & USAGE SECTION

- temporarily relieves minor aches and pains due to:
  - headache
  - toothache
  - backache
  - menstrual cramps
  - the common cold
  - muscular aches
  - minor pain of arthritis
- temporarily reduces fever

WARNINGS SECTION

Allergy alert: Ibuprofen may cause a severe allergic reaction, especially in people allergic to aspirin. Symptoms may include:

- hives
- facial swelling
- asthma (wheezing)
- shock
- skin reddening
- rash
- blisters

If an allergic reaction occurs, stop use and seek medical help right away.

Stomach bleeding warning: This product contains an NSAID, which may cause severe stomach bleeding. The chance is higher if you:

- have had stomach ulcers or bleeding problems
- take a blood thinning (anticoagulant) or steroid drug
- take other drugs containing prescription or nonprescription NSAIDs [aspirin, ibuprofen, naproxen, or others]
- have 3 or more alcoholic drinks every day while using this product
- take more or for a longer time than directed

Do not use

- right before or after heart surgery
- if you have ever had an allergic reaction to any other pain reliever/fever reducer

Ask a doctor before use if you have

- stomach bleeding warning applies to you
- you have a history of stomach problems, such as heartburn
- you have high blood pressure, heart disease, liver cirrhosis, or kidney disease
- you are taking a diuretic
- you have asthma
- you have problems or serious side effects from taking pain relievers or fever reducers

Ask a doctor or pharmacist before use if you are

- taking any other drug
- taking aspirin for heart attack or stroke, because ibuprofen may decrease this benefit of aspirin
- under a doctor"s care for any serious condition

When using this product

- take with food or milk if stomach upset occurs
- the risk of heart attack or stroke may increase if you use more than directed or for longer than directed

Stop use and ask a doctor if

- you experience any of the following signs of stomach bleeding:
  - feel faint
  - have bloody or black stools
  - vomit blood
  - have stomach pain that does not get better
- pain gets worse or lasts more than 10 days
- fever gets worse or lasts more than 3 days
- redness or swelling is present in the painful area
- any new symptoms appear

If pregnant or breast-feeding,

ask a health professional before use. It is especially important not to use ibuprofen during the last 3 months of pregnancy unless definitely directed to do so by a doctor because it may cause problems in the unborn child or complications during delivery.

Keep out of reach of children.

In case of overdose, get medical help or contact a Poison Control Center right away.

OTC - KEEP OUT OF REACH OF CHILDREN SECTION

Allergy alert: Ibuprofen may cause a severe allergic reaction, especially in people allergic to aspirin. Symptoms may include:

hives

facial swelling

asthma (wheezing)

shock

skin reddening

rash

blisters

If an allergic reaction occurs, stop use and seek medical help right away.

Stomach bleeding warning: This product contains an NSAID, which may cause severe stomach bleeding. The chance is higher if you:

have had stomach ulcers or bleeding problems

take a blood thinning (anticoagulant) or steroid drug

take other drugs containing prescription or nonprescription NSAIDs [aspirin, ibuprofen, naproxen, or others]

have 3 or more alcoholic drinks every day while using this product

take more or for a longer time than directed

Do not use

right before or after heart surgery

if you have ever had an allergic reaction to any other pain reliever/fever reducer

Ask a doctor before use if you have

stomach bleeding warning applies to you

you have a history of stomach problems, such as heartburn

you have high blood pressure, heart disease, liver cirrhosis, or kidney disease

you are taking a diuretic

you have asthma

you have problems or serious side effects from taking pain relievers or fever reducers

Ask a doctor or pharmacist before use if you are
taking any other drug
taking aspirin for heart attack or stroke, because ibuprofen may decrease this benefit of aspirin
under a doctor"s care for any serious condition

When using this product

take with food or milk if stomach upset occurs

the risk of heart attack or stroke may increase if you use more than directed or for longer than directed

Stop use and ask a doctor if

you experience any of the following signs of stomach bleeding:

feel faint

have bloody or black stools

vomit blood

have stomach pain that does not get better

pain gets worse or lasts more than 10 days

fever gets worse or lasts more than 3 days

redness or swelling is present in the painful area

any new symptoms appear

If pregnant or breast-feeding,

ask a health professional before use. It is especially important not to use ibuprofen during the last 3 months of pregnancy unless definitely directed to do so by a doctor because it may cause problems in the unborn child or complications during delivery.

Keep out of reach of children.

In case of overdose, get medical help or contact a Poison Control Center right away.

OTC - WHEN USING SECTION

- do not take more than directed
- the smallest effective dose should be used
- adults and children 12 years and over: take 1 tablet every 4 to 6 hours while symptoms persist
  - if pain or fever does not respond to 1 tablet, 2 tablets may be used
  - do not exceed 6 tablets in 24 hours, unless directed by a doctor
- children under 12 years: ask a doctor

INFORMATION FOR PATIENTS SECTION

- store between 20°-25°C (68°-77°F)
- avoid excessive heat 40°C (104°F)
- use by expiration date on package

DOSAGE & ADMINISTRATION SECTION

do not take more than directed

the smallest effective dose should be used

adults and children 12 years and over: take 1 tablet every 4 to 6 hours while symptoms persist
if pain or fever does not respond to 1 tablet, 2 tablets may be used

do not exceed 6 tablets in 24 hours, unless directed by a doctor

children under 12 years: ask a doctor

INACTIVE INGREDIENT SECTION

carnauba wax, corn starch, fumed silica gel, hypromellose, lactose, magnesium stearate, microcrystalline cellulose, polydextrose, polyethylene glycol, red iron oxide, sodium starch glycolate, stearic acid, titanium dioxide

OTC - QUESTIONS SECTION

(800) 616-2471